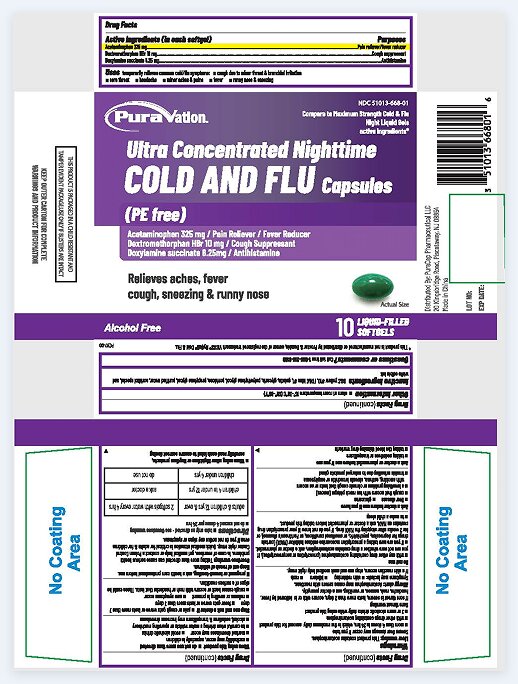 DRUG LABEL: Ultra Concentrated Nighttime COLD AND FLU
NDC: 51013-668 | Form: CAPSULE, LIQUID FILLED
Manufacturer: PuraCap Pharmaceutical LLC
Category: otc | Type: HUMAN OTC DRUG LABEL
Date: 20250311

ACTIVE INGREDIENTS: ACETAMINOPHEN 325 mg/1 1; DEXTROMETHORPHAN HYDROBROMIDE 10 mg/1 1; DOXYLAMINE SUCCINATE 6.25 mg/1 1
INACTIVE INGREDIENTS: D&C YELLOW NO. 10; FD&C BLUE NO. 1; GELATIN; GLYCERIN; POLYETHYLENE GLYCOL, UNSPECIFIED; POVIDONE; PROPYLENE GLYCOL; WATER; SORBITOL

Ultra Concentrated Nighttime COLD AND FLU Capsules

Drug Facts

Active ingredients (in each Softgel)

Acetaminophen 325 mg

Dextromethorphan HBr 10 mg

Doxylamine succinate 6.25 mg

Purposes

Pain reliever/fever reducer

Cough suppressant

Antihistamine

Uses

temporarily relieves common cold/flu symptoms:

- cough due to minor throat & bronchial irritation
- sore throat
- headache
- minor aches & pains
- fever
- runny nose & sneezing

Warnings

Liver warning

This product contains acetaminophen. Severe liver damage may occur if you take

- more than 4 doses in 24 hrs, which is the maximum daily amount for this product
- with other drugs containing acetaminophen
- 3 or more alcoholic drinks daily while using this product

Sore throat warning

If sore throat is severe, lasts more than 2 days, occurs with or is followed by fever, headache, rash, nausea, or vomiting, see a doctor promptly.

Allergy alert:Acetaminophen may cause severe skin reactions. Symptoms may include:

- skin reddening
- blisters
- rash

If a skin reaction occurs, stop use and seek medical help right away.

Do not use

- with any other drug containing acetaminophen (prescription or nonprescription). If you are not sure whether a drug contains acetaminophen, ask a doctor or pharmacist.
- if you are now taking a prescription monoamine oxidase inhibitor (MAOI) (certain drugs for depression, psychiatric, or emotional conditions, or Parkinson's disease), or for 2 weeks after stopping the MAOI drug. If you do not know if your prescription drug contains an MAOI, ask a doctor or pharmacist before taking this product.
- to make a child sleep

Ask a doctor before use if you have

- liver disease
- glaucoma
- cough that occurs with too much phlegm (mucus)
- a breathing problem or chronic cough that lasts or as occurs with smoking, asthma, chronic bronchitis or emphysema
- trouble urinating due to enlarged prostate gland

Ask a doctor or pharmacist before use if you are

- taking sedatives or tranquilizers
- taking the blood thinning drug warfarin

When using this product

- do not use more than directed
- excitability may occur, especially in children
- marked drowsiness may occur
- avoid alcoholic drinks
- be careful when driving a motor vehicle or operating machinery
- alcohol, sedatives & tranquilizers may increase drowsiness

Stop use and ask a doctor if

- pain or cough gets worse or lasts more than 7 days
- fever gets worse or lasts more than 3 days
- redness or swelling is present
- new symptoms occur
- cough comes back or occurs with rash or headache that lasts. These could be signs of a serious condition.

PREGNANCY OR BREAST FEEDING

If pregnant or breast-feeding,ask a health care professional before use.

Keep out of reach of children.

Overdose warning

Taking more than directed can cause serious health problems. In case of overdose, get medical help or contact a Poison Control Center right away. Quick medical attention is critical for adults & for children even if you do not notice any signs or symptoms.

Directions

- take only as directed - see Overdose warning
- do not exceed 4 doses per 24 hrs

adults & children 12 yrs & over | 2 softgels with water every 4 hrs
children 4 to under 12 yrs | ask a doctor
children under 4 yrs | do not use

- when using other Nighttime or Daytime products, carefully read each label to ensure correct dosing

Other information

- store at room temperature 15°-30°C (59°-86°F)

Inactive ingredients

D&C yellow #10, FD&C blue #1, gelatin, glycerin, polyethylene glycol, povidone, propylene glycol, purified water, sorbitol special, and white edible ink

Questions or comments?

Call toll free: 1-855-215-8180

PRINCIPAL DISPLAY PANEL

Nitetime Cold & Flu 10 SOFTGELS

NDC 51013-668-01

*Compare to the active ingredients in VICKS®NyQuil®Cold & Flu